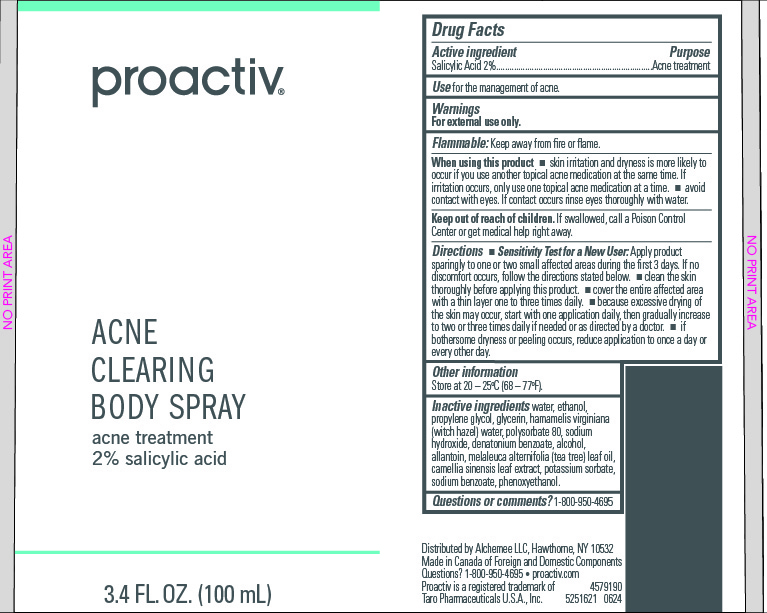 DRUG LABEL: Proactiv Acne Clearing Body
NDC: 11410-217 | Form: SPRAY
Manufacturer: Alchemee, LLC
Category: otc | Type: HUMAN OTC DRUG LABEL
Date: 20260107

ACTIVE INGREDIENTS: SALICYLIC ACID 2 mg/100 mL
INACTIVE INGREDIENTS: GLYCERIN; POLYSORBATE 80; DENATONIUM BENZOATE; ALCOHOL; HAMAMELIS VIRGINIANA TOP WATER; SODIUM HYDROXIDE; TEA TREE OIL; GREEN TEA LEAF; WATER; PHENOXYETHANOL; POTASSIUM SORBATE; SODIUM BENZOATE; PROPYLENE GLYCOL; ALLANTOIN

Proactiv Acne Clearing Body Spray

Drug Facts

Active ingredient

Salicylic Acid 2%

Purpose

Acne treatment

Use

for the management of acne

Warnings

For external use only

When using this product

- skin irritation and dryness is more likely to occur if you use another topical acne medication at the same time. If irritation occurs, only use one topical acne medication at a time.
- avoid contact with eyes. if contact occurs rinse eyes thoroughly with water.

Keep out of reach of children.

If swallowed, get medical help or contact a Poison Control Center right away.

Directions

- Sensitivity Test for a New User. Apply product sparingly to one or two small affected areas during the first 3 days. If no discomfort occurs, follow the directions stated below.
- clean the skin thoroughly before applying this product.
- cover the entire affected area with a thin layer and rinse thoroughly one to three times daily
- because excessive drying of the skin may occur, start with one application daily, then gradually increase to two or three times daily if needed or as directed by a doctor
- if bothersome dryness or peeling occurs, reduce application to once a day or every other day

Other Information

Store at 20-25°C (68 - 77°F)

Inactive ingredients

Water, Ethanol, Propylene Glycol, Glycerin, Hamamelis Virginiana (Witch Hazel) Water, Polysorbate 80, Sodium Hydroxide, Denatonium Benzoate, Alcohol, Allantoin, Melaleuca Alternifolia (Tea Tree) Leaf Oil, Camellia Sinensis Leaf Extract, Potassium Sorbate, Sodium Benzoate, Phenoxyethanol.

Questions or comments?

1-800-950-4695

Distributed by Alchemee LLC, Hawthorne, NY 10532
Made in the USA of Foreign and Domestic Components
Questions? 1-800-950-4695 • proactiv.com • Proactiv is a
registered trademark of Taro Pharmaceuticals U.S.A., Inc.

PRINCIPAL DISPLAY PANEL - 60 mL Carton

proactiv

ACNE

CLEARING

BODY SPRAY

ACNE TREATMENT

2% salicylic acid

3.4 FL. OZ. (100 mL)